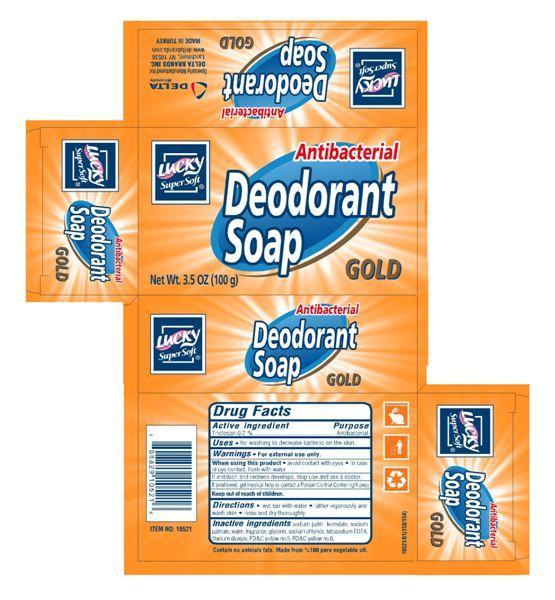 DRUG LABEL: Lucky
NDC: 20276-050 | Form: SOAP
Manufacturer: Delta Brands Inc.
Category: otc | Type: HUMAN OTC DRUG LABEL
Date: 20130408

ACTIVE INGREDIENTS: TRICLOSAN 0.2 g/100 g
INACTIVE INGREDIENTS: SODIUM PALM KERNELATE; SODIUM PALMITATE; WATER; GLYCERIN; SODIUM CHLORIDE; EDETATE SODIUM; TITANIUM DIOXIDE; FD&C YELLOW NO. 5; FD&C YELLOW NO. 6

Drug Facts

Active ingredient
Triclosan 0.2%

Purpose
Antibacterial

INDICATIONS AND USAGE

Uses • for hand washing to decrease bacteria on the skin.

Warnings • For external use only

When using this product • avoid contact with eyes • in case of eye contact, flush with water.

STOP USE

If irritation and redness develops, stop use and ask a doctor

KEEP OUT OF REACH OF CHILDREN

If swallowed get medical help or contact a Poison Control Center right away. Keep out of the reach of children.

DOSAGE AND ADMINISTRATION

Directions •wet bar with water • lather vigorously and wash skin • rinse and dry thoroughly.

INACTIVE INGREDIENT

Inactive ingredients sodium palm kernelate, sodium palmate, water, fragrance, glycerin, sodium chloride, tetrasodium EDTA, titanium dioxide, FDC yellow no. 5, FDC yellow no. 6